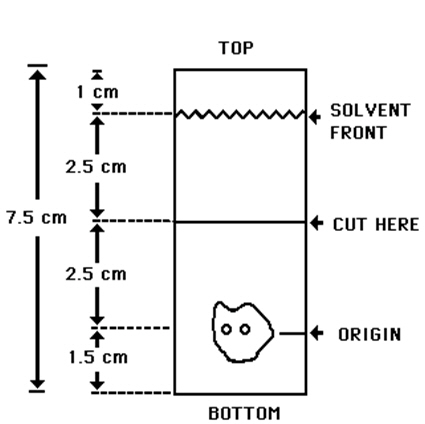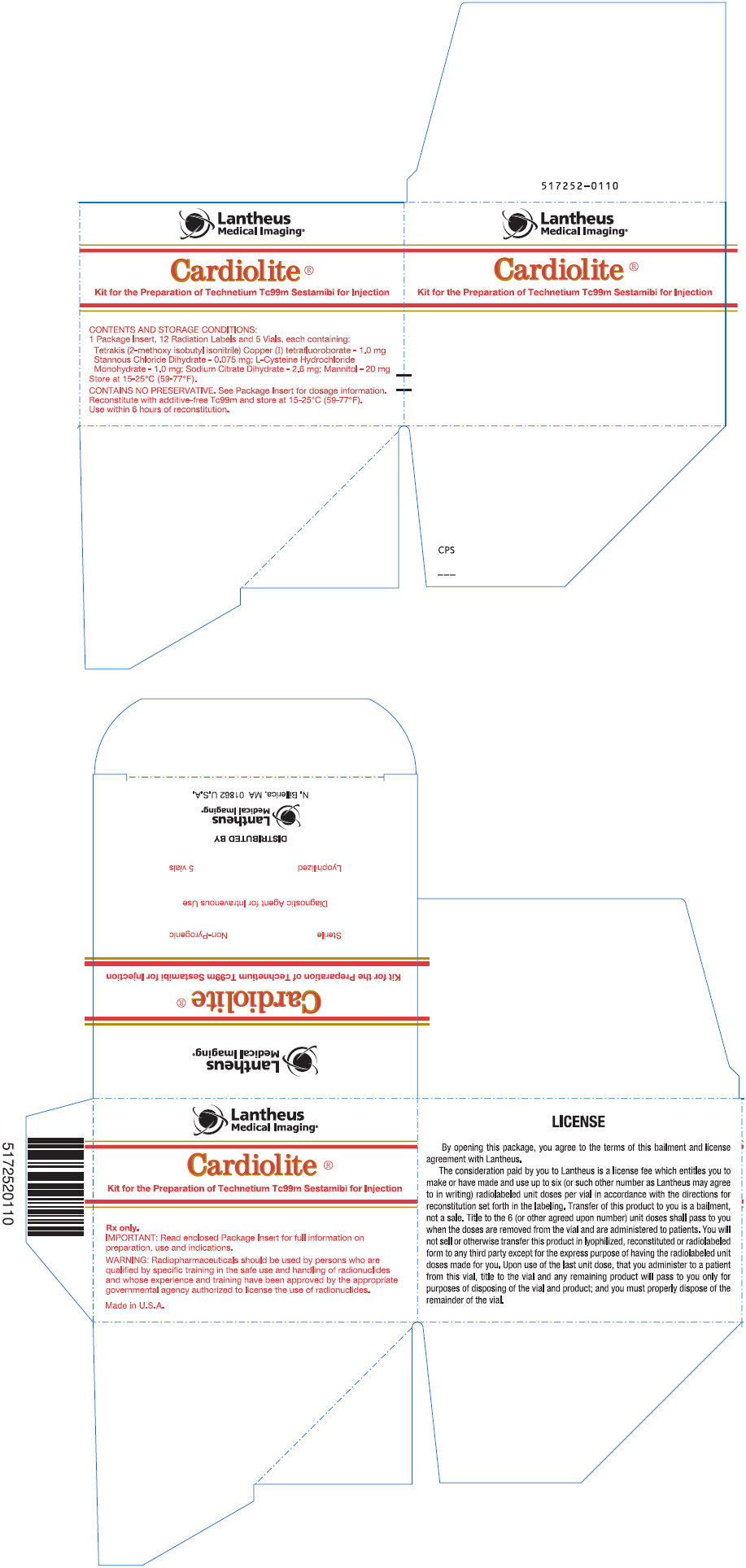 DRUG LABEL: Cardiolite
NDC: 11994-001 | Form: INJECTION, POWDER, LYOPHILIZED, FOR SOLUTION
Manufacturer: Lantheus Medical Imaging, Inc.
Category: prescription | Type: HUMAN PRESCRIPTION DRUG LABEL
Date: 20221206

ACTIVE INGREDIENTS: TETRAKIS(2-METHOXYISOBUTYLISOCYANIDE)COPPER(I) TETRAFLUOROBORATE 1 mg/1 mL
INACTIVE INGREDIENTS: TRISODIUM CITRATE DIHYDRATE 2.6 mg/1 mL; CYSTEINE HYDROCHLORIDE 1 mg/1 mL; MANNITOL 20 mg/1 mL; STANNOUS CHLORIDE 0.075 mg/1 mL

HIGHLIGHTS OF PRESCRIBING INFORMATION

These highlights do not include all the information needed to use CARDIOLITE® safely and effectively. See full prescribing information for CARDIOLITE®.
CARDIOLITE®, Kit for the Preparation of Technetium Tc99m Sestamibi for Injection
Initial U.S. Approval: December, 1990

1. INDICATIONS AND USAGE

CARDIOLITE® is a myocardial perfusion agent indicated for:

- detecting coronary artery disease by localizing myocardial ischemia (reversible defects) and infarction (non-reversible defects)
- evaluating myocardial function and developing information for use in patient management decisions

2. DOSAGE AND ADMINISTRATION

- For Myocardial Imaging: The suggested dose range for I.V. administration of CARDIOLITE® in a single dose to be employed in the average patient (70 Kg) is 370 - 1110 MBq (10 - 30 mCi).
- For Breast Imaging: The recommended dose range for I.V. administration of MIRALUMA® is a single dose of 740 - 1110 MBq (20 - 30 mCi).

3. DOSAGE FORMS AND STRENGTHS

CARDIOLITE®, Kit for the Preparation of Technetium Tc99m Sestamibi for Injection is supplied as a lyophilized mixture in a 5 mL vial.

4. CONTRAINDICATIONS

- None known.

5. WARNINGS AND PRECAUTIONS

- Pharmacologic induction of cardiovascular stress may be associated with serious adverse events such as myocardial infarction, arrhythmia, hypotension, bronchoconstriction and cerebrovascular events.
- CARDIOLITE® has been rarely associated with acute severe allergic and anaphylactic events of angioedema and generalized urticaria. In some patients the allergic symptoms developed on the second injection during CARDIOLITE® imaging.
- Caution should be exercised and emergency equipment should be available when administering CARDIOLITE®.
- Before administering CARDIOLITE® patients should be asked about the possibility of allergic reactions to either drug.
- The contents of the vial are intended only for use in the preparation of Technetium Tc99m Sestamibi and are not to be administered directly to the patient without first undergoing the preparative procedure.

6. ADVERSE REACTIONS

The following adverse reactions have been reported in ≤ 0.5% of patients: signs and symptoms consistent with seizure occurring shortly after administration of the agent; transient arthritis, angioedema, arrythmia, dizziness, syncope, abdominal pain, vomiting, and severe hypersensitivity characterized by dyspnea, hypotension, bradycardia, asthenia, and vomiting within two hours after a second injection of Technetium Tc99m Sestamibi. A few cases of flushing, edema, injection site inflammation, dry mouth, fever, pruritis, rash, urticaria and fatigue have also been attributed to administration of the agent.

To report SUSPECTED ADVERSE REACTIONS, contact Lantheus Medical Imaging, Inc. at 1-800-362-2668 or FDA at 1-800-FDA-1088 or www.fda.gov/medwatch.

7. DRUG INTERACTIONS

- Specific drug-drug interactions have not been studied.

8. USE IN SPECIFIC POPULATIONS

- In one study of 46 subjects who received CARDIOLITE® administration, the radioactivity in both children and adolescents exhibited blood PK profiles similar to those previously reported in adults.
- Lactation: Interruption of breastfeeding after exposure to Technetium Tc99m Sestamibi is not necessary, however, a lactating woman should be advised to consider restricting close contact with her breast fed infant to a maximum of 5 hours in the 24 hour period after Technetium Tc99m Sestamibi administration in order to minimize radiation exposure. (8.2)

FULL PRESCRIBING INFORMATION

1. INDICATIONS AND USAGE

Myocardial Imaging: CARDIOLITE®, Kit for the Preparation of Technetium Tc99m Sestamibi for Injection, is a myocardial perfusion agent that is indicated for detecting coronary artery disease by localizing myocardial ischemia (reversible defects) and infarction (non-reversible defects), in evaluating myocardial function and developing information for use in patient management decisions. CARDIOLITE® evaluation of myocardial ischemia can be accomplished with rest and cardiovascular stress techniques (e.g., exercise or pharmacologic stress in accordance with the pharmacologic stress agent's labeling).

It is usually not possible to determine the age of a myocardial infarction or to differentiate a recent myocardial infarction from ischemia.

Breast Imaging: MIRALUMA®, Kit for the Preparation of Technetium Tc99m Sestamibi for Injection, is indicated for planar imaging as a second line diagnostic drug after mammography to assist in the evaluation of breast lesions in patients with an abnormal mammogram or a palpable breast mass.

MIRALUMA® is not indicated for breast cancer screening, to confirm the presence or absence of malignancy, and it is not an alternative to biopsy.

2. DOSAGE AND ADMINISTRATION

For Myocardial Imaging: The suggested dose range for I.V. administration of CARDIOLITE® in a single dose to be employed in the average patient (70 Kg) is 370 - 1110 MBq (10 - 30 mCi).

For Breast Imaging: The recommended dose range for I.V. administration of MIRALUMA® is a single dose of 740 - 1110 MBq (20 - 30 mCi).

2.1 Image Acquisition

Breast Imaging: It is recommended that images are obtained with a table overlay to separate breast tissue from the myocardium and liver, and to exclude potential activity that may be present in the opposite breast. For lateral images, position the patient prone with the isolateral arm comfortably above the head, shoulders flat against the table, head turned to the side and relaxed, with the breast imaged pendent through an overlay cutout. The breast should not be compressed on the overlay. For anterior images, position the patient supine with both arms behind the head. For either lateral or anterior images, shield the chest and abdominal organs, or remove them from the field of view.

For complete study, sets of images should be obtained five minutes after the injection, and in the following sequence:

Beginning five minutes after the injection of Technetium Tc99m Sestamibi:

- ten-minute lateral image of breast with abnormality
- ten-minute lateral image of contralateral breast
- ten-minute anterior image of both breasts

2.2 Radiation Dosimetry

The radiation doses to organs and tissues of an average patient (70 Kg) per 1110 MBq (30 mCi) of Technetium Tc99m Sestamibi injected intravenously are shown in Table 1.0.

Table 1.0. Radiation Absorbed Doses from Tc99m Sestamibi
 | Estimated Radiation Absorbed Dose
 | REST
 | 2.0 hour void |  | 4.8 hour void
Organ | rads/ 30 mCi | mGy/ 1110 MBq | rads/ 30 mCi | mGy/ 1110 MBq
Breasts | 0.2 | 2.0 | 0.2 | 1.9
Gallbladder Wall | 2.0 | 20.0 | 2.0 | 20.0
Small Intestine | 3.0 | 30.0 | 3.0 | 30.0
Upper Large Intestine Wall | 5.4 | 55.5 | 5.4 | 55.5
Lower Large Intestine Wall | 3.9 | 40.0 | 4.2 | 41.1
Stomach Wall | 0.6 | 6.1 | 0.6 | 5.8
Heart Wall | 0.5 | 5.1 | 0.5 | 4.9
Kidneys | 2.0 | 20.0 | 2.0 | 20.0
Liver | 0.6 | 5.8 | 0.6 | 5.7
Lungs | 0.3 | 2.8 | 0.3 | 2.7
Bone Surfaces | 0.7 | 6.8 | 0.7 | 6.4
Thyroid | 0.7 | 7.0 | 0.7 | 7.0
Ovaries | 1.5 | 15.5 | 1.6 | 15.5
Testes | 0.3 | 3.4 | 0.4 | 3.9
Red Marrow | 0.5 | 5.1 | 0.5 | 5.0
Urinary Bladder Wall | 2.0 | 20.0 | 4.2 | 41.1
Total Body | 0.5 | 4.8 | 0.5 | 4.8
 | STRESS
 | 2.0 hour void |  | 4.8 hour void
Organ | rads/ 30 mCi | mGy/ 1110 MBq | rads/ 30 mCi | mGy/ 1110 MBq
Breasts | 0.2 | 2.0 | 0.2 | 1.8
Gallbladder Wall | 2.8 | 28.9 | 2.8 | 27.8
Small Intestine | 2.4 | 24.4 | 2.4 | 24.4
Upper Large Intestine Wall | 4.5 | 44.4 | 4.5 | 44.4
Lower Large Intestine Wall | 3.3 | 32.2 | 3.3 | 32.2
Stomach Wall | 0.6 | 5.3 | 0.5 | 5.2
Heart Wall | 0.5 | 5.6 | 0.5 | 5.3
Kidneys | 1.7 | 16.7 | 1.7 | 16.7
Liver | 0.4 | 4.2 | 0.4 | 4.1
Lungs | 0.3 | 2.6 | 0.2 | 2.4
Bone Surfaces | 0.6 | 6.2 | 0.6 | 6.0
Thyroid | 0.3 | 2.7 | 0.2 | 2.4
Ovaries | 1.2 | 12.2 | 1.3 | 13.3
Testes | 0.3 | 3.1 | 0.3 | 3.4
Red Marrow | 0.5 | 4.6 | 0.5 | 4.4
Urinary Bladder Wall | 1.5 | 15.5 | 3.0 | 30.0
Total Body | 0.4 | 4.2 | 0.4 | 4.2
Radiation dosimetry calculations performed by Radiation Internal Dose Information Center, Oak Ridge Institute for Science and Education, PO Box 117, Oak Ridge, TN 37831-0117.

2.3 Instructions For Preparation

Preparation of the Technetium Tc99m Sestamibi from the Kit for the Preparation of Technetium Tc99m Sestamibi is done by the following aseptic procedure:

General Procedure:

a. Prior to adding the Sodium Pertechnetate Tc99m Injection to the vial, inspect the vial carefully for the presence of damage, particularly cracks, and do not use the vial if found. Tear off a radiation symbol and attach it to the neck of the vial.
b. Waterproof gloves should be worn during the preparation procedure. Remove the plastic disc from the vial and swab the top of the vial closure with alcohol to sanitize the surface.

Boiling Water Bath Procedure:

c. Place the vial in a suitable radiation shield with a fitted radiation cap.
d. With a sterile shielded syringe, aseptically obtain additive-free, sterile, non-pyrogenic Sodium Pertechnetate Tc99m Injection [925 - 5550 MBq, (25 - 150 mCi)] in approximately 1 to 3 mL.
e. Aseptically add the Sodium Pertechnetate Tc99m Injection to the vial in the lead shield. Without withdrawing the needle, remove an equal volume of headspace to maintain atmospheric pressure within the vial.
f. Shake vigorously, about 5 to 10 quick upward-downward motions.
g. Remove the vial from the lead shield and place upright in an appropriately shielded and contained boiling water bath, such that the vial is suspended above the bottom of the bath, and boil for 10 minutes. Timing for 10 minutes is begun as soon as the water begins to boil again. Do not allow the boiling water to come in contact with the aluminum crimp.
h. Remove the vial from the water bath, place in the lead shield and allow to cool for fifteen minutes.

Recon-o-Stat (thermal cycler) Procedure:

c. Place the vial in the thermal cycler radiation shield.
d. With a sterile shielded syringe, aseptically obtain additive-free, sterile, non-pyrogenic Sodium Pertechnetate Tc99m Injection [925 - 5550 MBq, (25 - 150 mCi)] in approximately 1 to 3 mL.
e. Aseptically add the Sodium Pertechnetate Tc99m Injection to the vial in the lead shield. Without withdrawing the needle, remove an equal volume of headspace to maintain atmospheric pressure within the vial.
f. Shake vigorously, about 5 to 10 quick upward-downward motions.
g. Place shield on sample block. While slightly pressing downward, give the shield a quarter turn to make certain there is a firm fit between the shield and the sample block.
h. Press the proceed button to initiate the program (the thermal cycler automatically heats & cools the vial and contents). Please see the Recon-o-Stat Instruction Manual for further details.

General Procedure (cont.):

i. Using proper shielding, the vial contents should be visually inspected. Use only if the solution is clear and free of particulate matter and discoloration.
j. Assay the reaction vial using a suitable radioactivity calibration system. Record the Technetium Tc99m concentration, total volume, assay time and date, expiration time and lot number on the vial shield label and affix the label to the shield.
k. Store the reaction vial containing the Technetium Tc99m Sestamibi at 15° to 25°C (59° - 77°F) until use; at such time the product should be aseptically withdrawn. Technetium Tc99m Sestamibi should be used within six hours of preparation. The vial contains no preservative.

Note:

Adherence to the above product reconstitution instructions is recommended.

The potential for cracking and significant contamination exists whenever vials containing radioactive material are heated.

Product should be used within 6 hours after preparation.

Final product with radiochemical purity of at least 90% was used in the clinical trials that established safety and effectiveness. The radiochemical purity was determined by the following method.

2.4 Determination of Radiochemical Purity in Technetium Tc99m Sestamibi

1. Obtain a Baker-Flex Aluminum Oxide coated, plastic TLC plate, #1 B-F, pre-cut to 2.5 cm × 7.5 cm.
2. Dry the plate or plates at 100°C for 1 hour and store in a desiccator. Remove pre-dried plate from the desiccator just prior to use.
3. Apply 1 drop of ethanol [The ethanol used in this procedure should be 95% or greater. Absolute ethanol (99%) should remain at ≥ 95% ethanol content for one week after opening if stored tightly capped, in a cool dry place.] using a 1 mL syringe with a 22-26 gauge needle, 1.5 cm from the bottom of the plate. THE SPOT SHOULD NOT BE ALLOWED TO DRY.
4. Add 2 drops of Technetium Tc99m Sestamibi solution, side by side on top of the ethanol spot. Return the plate to a desiccator and allow the sample spot to dry (typically 15 minutes).
5. The TLC tank is prepared by pouring ethanol to a depth of 3-4 mm. Cover the tank and let it equilibrate for ~10 minutes.
6. Develop the plate in the covered TLC tank in ethanol for a distance of 5 cm from the point of application.
7. Cut the TLC plate 4 cm from the bottom and measure the Tc99m activity in each piece by appropriate radiation detector.
8. Calculate the % Tc99m Sestamibi as:
  % Tc99m Sestamibi = | µCi Top Piece | × 100
   | µCi Both Pieces

Figure 1.0 TLC Plate Diagram

3. DOSAGE FORMS AND STRENGTHS

CARDIOLITE®, Kit for the Preparation of Technetium Tc99m Sestamibi for Injection is supplied as a lyophilized mixture in a 5 mL vial.

4. CONTRAINDICATIONS

None known.

5. WARNINGS AND PRECAUTIONS

5.1 Warnings

In studying patients in whom cardiac disease is known or suspected, care should be taken to assure continuous monitoring and treatment in accordance with safe, accepted clinical procedure. Infrequently, death has occurred 4 to 24 hours after Tc99m Sestamibi use and is usually associated with exercise stress testing (See Section 5.2).

Pharmacologic induction of cardiovascular stress may be associated with serious adverse events such as myocardial infarction, arrhythmia, hypotension, bronchoconstriction and cerebrovascular events. Caution should be used when pharmacologic stress is selected as an alternative to exercise; it should be used when indicated and in accordance with the pharmacologic stress agent's labeling.

Technetium Tc99m Sestamibi has been rarely associated with acute severe allergic and anaphylactic events of angioedema and generalized urticaria. In some patients the allergic symptoms developed on the second injection during CARDIOLITE® imaging. Patients who receive CARDIOLITE® or MIRALUMA® imaging are receiving the same drug. Caution should be exercised and emergency equipment should be available when administering Technetium Tc99m Sestamibi. Also, before administering either CARDIOLITE® or MIRALUMA®, patients should be asked about the possibility of allergic reactions to either drug.

5.2 General Precautions

The contents of the vial are intended only for use in the preparation of Technetium Tc99m Sestamibi and are not to be administered directly to the patient without first undergoing the preparative procedure.

Radioactive drugs must be handled with care and appropriate safety measures should be used to minimize radiation exposure to clinical personnel. Also, care should be taken to minimize radiation exposure to the patients consistent with proper patient management.

Contents of the kit before preparation are not radioactive. However, after the Sodium Pertechnetate Tc99m Injection is added, adequate shielding of the final preparation must be maintained. The components of the kit are sterile and non-pyrogenic. It is essential to follow directions carefully and to adhere to strict aseptic procedures during preparation.

Technetium Tc99m labeling reactions depend on maintaining the stannous ion in the reduced state. Hence, Sodium Pertechnetate Tc99m Injection containing oxidants should not be used.

Technetium Tc99m Sestamibi should not be used more than six hours after preparation.

Radiopharmaceuticals should be used only by physicians who are qualified by training and experience in the safe use and handling of radionuclides and whose experience and training have been approved by the appropriate government agency authorized to license the use of radionuclides.

Stress testing should be performed only under the supervision of a qualified physician and in a laboratory equipped with appropriate resuscitation and support apparatus.

The most frequent exercise stress test endpoints sufficient to stop the test reported during controlled studies (two-thirds were cardiac patients) were:

Fatigue | 35%
Dyspnea | 17%
Chest Pain | 16%
ST-depression | 7%
Arrhythmia | 1%

6. ADVERSE REACTIONS

Adverse events were evaluated in 3741 adults who were evaluated in clinical studies. Of these patients, 3068 (77% men, 22% women, and 0.7% of the patient's genders were not recorded) were in cardiac clinical trials and 673 (100% women) in breast imaging trials. Cases of angina, chest pain, and death have occurred (see Section 5). Adverse events reported at a rate of 0.5% or greater after receiving Technetium Tc99m Sestamibi administration are shown in the following table:

Table 2.0 Selected Adverse Events Reported in > 0.5% of Patients Who Received Technetium Tc99m Sestamibi in Either Breast or Cardiac Clinical Studies [Excludes the 22 patients whose gender was not recorded.]
Body System | Breast Studies | Cardiac Studies
 | Women n = 673 | Women n = 685 | Men n = 2361 | Total n = 3046
Body as a Whole | 21 (3.1%) | 6 (0.9%) | 17 (0.7%) | 23 (0.8%)
Headache | 11 (1.6%) | 2 (0.3%) | 4 (0.2%) | 6 (0.2%)
Cardiovascular | 9 (1.3%) | 24 (3.5%) | 75 (3.2%) | 99 (3.3%)
Chest Pain/Angina | 0 (0%) | 18 (2.6%) | 46 (1.9%) | 64 (2.1%)
ST segment changes | 0 (0%) | 11 (1.6%) | 29 (1.2%) | 40 (1.3%)
Digestive System | 8 (1.2%) | 4 (0.6%) | 9 (0.4%) | 13 (0.4%)
Nausea | 4 (0.6%) | 1 (0.1%) | 2 (0.1%) | 3 (0.1%)
Special Senses | 132 (19.6%) | 62 (9.1%) | 160 (6.8%) | 222 (7.3%)
Taste Perversion | 129 (19.2%) | 60 (8.8%) | 157 (6.6%) | 217 (7.1%)
Parosmia | 8 (1.2%) | 6 (0.9%) | 10 (0.4%) | 16 (0.5%)

In the clinical studies for breast imaging, breast pain was reported in 12 (1.7%) of the patients. In 11 of these patients the pain appears to be associated with biopsy/surgical procedures.

The following adverse reactions have been reported in ≤ 0.5% of patients: signs and symptoms consistent with seizure occurring shortly after administration of the agent; transient arthritis, angioedema, arrythmia, dizziness, syncope, abdominal pain, vomiting, and severe hypersensitivity characterized by dyspnea, hypotension, bradycardia, asthenia, and vomiting within two hours after a second injection of Technetium Tc99m Sestamibi. A few cases of flushing, edema, injection site inflammation, dry mouth, fever, pruritis, rash, urticaria and fatigue have also been attributed to administration of the agent.

7. DRUG INTERACTIONS

Specific drug-drug interactions have not been studied.

8. USE IN SPECIFIC POPULATIONS

8.1 Pregnancy

Risk Summary

Limited available data with Technetium Tc99m Sestamibi use in pregnant women have not identified a drug-associated risk of major birth defects, miscarriage, or adverse maternal or fetal outcomes. Animal reproduction and teratogenicity studies have not been conducted with Technetium Tc99m Sestamibi. However, all radiopharmaceuticals have the potential to cause fetal harm depending on the fetal stage of development and the magnitude of the radiation dose. If considering Technetium Tc99m Sestamibi administration to a pregnant woman, inform the patient about the potential for adverse pregnancy outcomes based on the radiation dose from Technetium Tc99m Sestamibi and the gestational timing of exposure.

All pregnancies have a background risk of birth defects, loss, or other adverse outcomes. In the U.S. general population, the estimated background risk of major birth defects and miscarriage in clinically recognized pregnancies is 2-4% and 15-20%, respectively.

8.2 Lactation

Risk Summary

Limited data in the scientific literature on the presence of Technetium Tc99m Sestamibi in human milk, demonstrate that between 0.01% and 0.03% of maternal injected activity of technetium Tc99m Sestamibi was excreted in human milk. Technetium Tc99m Sestamibi accumulates in the lactating breast [see Clinical Considerations]. There are limited data in the scientific literature on effects of Technetium Tc99m Sestamibi on the breastfed infant or on milk production The developmental and health benefits of breastfeeding should be considered along with the mother's clinical need for Technetium Tc99m Sestamibi and any potential adverse effects on the breastfed infant from Technetium Tc99m Sestamibi or from the underlying maternal condition.

Clinical Considerations

Interruption of breastfeeding after exposure to Technetium Tc99m Sestamibi is not necessary because Technetium Tc99m Sestamibi excretion in breast milk is low. However, a lactating woman may restrict close contact with her breast fed infant to a maximum of 5 hours in the 24 hour period after Technetium Tc99m Sestamibi administration in order to minimize radiation exposure.

8.4 Pediatric Use

Safety and effectiveness in the pediatric population have not been established.

No evidence of diagnostic efficacy or clinical utility of CARDIOLITE® scan was found in clinical studies of children and adolescents with Kawasaki disease.

A prospective study of 445 pediatric patients with Kawasaki disease was designed to determine the predictive value of CARDIOLITE® rest and stress myocardial perfusion imaging to define a pediatric population with Kawasaki disease that was at risk of developing cardiac events. Cardiac events were defined as cardiac death, MI, hospitalization due to cardiac etiology, heart failure, CABG or coronary angioplasty. The standard of truth was defined as cardiac events occurring 6 months following the administration of CARDIOLITE®. Only three cardiac events were observed at six months in this study. In all three cases, the scan was negative. No clinically meaningful measurements of sensitivity, specificity or other diagnostic performance parameters could be demonstrated in this study.

A ten year retrospective case history study of pediatric Kawasaki disease patients who completed CARDIOLITE® myocardial perfusion imaging and who had coronary angiography within three months of the CARDIOLITE® scan was designed to measure sensitivity and specificity of CARDIOLITE® scan. Out of 72 patients who had both evaluable CARDIOLITE® scans and evaluable angiographic images, only one patient had both an abnormal angiogram and an abnormal CARDIOLITE® scan. No clinically meaningful measurements of sensitivity, specificity or other diagnostic performance parameters could be demonstrated in this study.

In a clinical pharmacology study, 46 pediatric patients with Kawasaki disease received CARDIOLITE® administration at the following doses: 0.1 - 0.2 mCi/kg for rest, 0.3 mCi/kg for stress in one day studies; 0.2 mCi/kg for rest and 0.2 mCi/kg for stress in two day studies.

The radioactivity both in younger children and in adolescents exhibited PK profiles similar to those previously reported in adults (See Section 12).

The radiation absorbed doses in adolescents, both at rest and stress, were similar to those observed in adults (see Section 2). When comparing weight-adjusted radioactivity (up to 0.3 mCi/kg) doses administered to adolescents and younger children to the recommended dose administered to adults (up to 30 mCi), the radiation absorbed doses in both adolescents and younger children were similar to those in adults.

Adverse events were evaluated in 609 pediatric patients from the three clinical studies described above. The frequency and the type of the adverse events were similar to the ones observed in the studies of CARDIOLITE® in adults. Two of the 609 had a serious adverse event: one patient received a CARDIOLITE® overdose but remained asymptomatic, and one patient had an asthma exacerbation following administration.

8.5 Geriatric Use

Of 3068 patients in clinical studies of CARDIOLITE®, Kit for the Preparation of Technetium Tc99m Sestamibi for Injection, 693 patients were 65 or older and 121 were 75 or older.

Of 673 patients in clinical studies of MIRALUMA®, Kit for the Preparation of Technetium Tc99m Sestamibi for Injection, 138 patients were 65 or older and 30 were 75 or older.

Based on the evaluation of the frequency of adverse events and review of vital signs data, no overall differences in safety were observed between these subjects and younger subjects. Although reported clinical experience has not identified differences in response between elderly and younger patients, greater sensitivity of some older individuals cannot be ruled out.

10. OVERDOSAGE

The clinical consequences of overdosing with CARDIOLITE® are not known.

11. DESCRIPTION

Each 5 mL vial contains a sterile, non-pyrogenic, lyophilized mixture of:

- Tetrakis (2-methoxy isobutyl isonitrile) Copper (I) tetrafluoroborate - 1.0 mg
- Sodium Citrate Dihydrate - 2.6 mg
- L-Cysteine Hydrochloride Monohydrate - 1.0 mg
- Mannitol – 20 mg
- Stannous Chloride, Dihydrate, minimum (SnCl2∙2H2O) - 0.025 mg
- Stannous Chloride, Dihydrate, (SnCl2∙2H2O) - 0.075 mg
- Tin Chloride (stannous and stannic) Dihydrate, maximum (as SnCl2∙2H2O) - 0.086 mg

Prior to lyophilization the pH is 5.3 to 5.9. The contents of the vial are lyophilized and stored under nitrogen.

This drug is administered by intravenous injection for diagnostic use after reconstitution with sterile, non-pyrogenic, oxidant-free Sodium Pertechnetate Tc99m Injection. The pH of the reconstituted product is 5.5 (5.0 - 6.0). No bacteriostatic preservative is present.

The precise structure of the technetium complex is Tc99m[MIBI]6^+ where MIBI is 2-methoxy isobutyl isonitrile.

11.1 Physical Characteristics

Technetium Tc99m decays by isomeric transition with a physical half-life of 6.02 hours [Kocher, David, C., Radioactive Decay Data Tables, DOE/TIC-11026, 108(1981).] . Photons that are useful for detection and imaging studies are listed below in Table 3.0.

Table 3.0. Principal Radiation Emission Data
Radiation | Mean %/Disintegration | Mean Energy (KeV)
Gamma -2 | 89.07 | 140.5

11.2 External Radiation

The specific gamma ray constant for Tc99m is 5.4 microcoulombs/Kg-MBq-hr (0.78R/mCi-hr) at 1 cm. The first half value layer is 0.017 cm of Pb. A range of values for the relative attenuation of the radiation emitted by this radionuclide that results from interposition of various thicknesses of Pb is shown in Table 4.0. To facilitate control of the radiation exposure from Megabequerel (millicurie) amounts of this radionuclide, the use of a 0.25 cm thickness of Pb will attenuate the radiation emitted by a factor of 1,000.

Table 4.0. Radiation Attenuation by Lead Shielding
Shield Thickness (Pb) cm | Coefficient of Attenuation
0.017 | 0.5
0.08 | 10^-1
0.16 | 10^-2
0.25 | 10^-3
0.33 | 10^-4

To correct for physical decay of this radionuclide, the fractions that remain at selected intervals after the time of calibration are shown in Table 5.0.

Table 5.0 Physical Decay Chart; Tc99m Half-Life 6.02 Hours
Hours | Fraction Remaining | Hours | Fraction Remaining
0 [Calibration Time] | 1.000 | 8 | .398
1 | .891 | 9 | .355
2 | .794 | 10 | .316
3 | .708 | 11 | .282
4 | .631 | 12 | .251
5 | .562
6 | .501
7 | .447

12. CLINICAL PHARMACOLOGY

12.1 Mechanism of Action

Technetium Tc99m Sestamibi is a cationic Tc99m complex which has been found to accumulate in viable myocardial tissue in a manner analogous to that of thallous chloride Tl-201. Scintigraphic images obtained in humans after the intravenous administration of the drug have been comparable to those obtained with thallous chloride Tl-201 in normal and abnormal myocardial tissue.

Animal studies have shown that myocardial uptake is not blocked when the sodium pump mechanism is inhibited. Although studies of subcellular fractionation and electron micrographic analysis of heart cell aggregates suggest that Tc99m Sestamibi cellular retention occurs specifically within the mitochondria as a result of electrostatic interactions, the clinical relevance of these findings has not been determined.

The mechanism of Tc99m Sestamibi localization in various types of breast tissue (e.g., benign, inflammatory, malignant, fibrous) has not been established.

12.3 Pharmacokinetics

Pulmonary activity is negligible even immediately after injection. Blood clearance studies indicate that the fast clearing component clears with a t1/2 of 4.3 minutes at rest, and clears with a t1/2 of 1.6 minutes under exercise conditions. At five minutes post injection about 8% of the injected dose remains in circulation. There is less than 1% protein binding of Technetium Tc99m Sestamibi in plasma. The myocardial biological half-life is approximately six hours after a rest or exercise injection. The biological half-life for the liver is approximately 30 minutes after a rest or exercise injection. The effective half-life of clearance (which includes both the biological half-life and radionuclide decay) for the heart is approximately 3 hours, and for the liver is approximately 30 minutes, after a rest or exercise injection. The ideal imaging time reflects the best compromise between heart count rate and surrounding organ uptake.

Myocardial uptake which is coronary flow dependent is 1.2% of the injected dose at rest and 1.5% of the injected dose at exercise. Table 6.0 illustrates the biological clearance as well as effective clearance (which includes biological clearance and radionuclide decay) of Tc99m Sestamibi from the heart and liver.

[Organ concentrations expressed as percentage of injected dose; data based on an average of 5 subjects at rest and 5 subjects during exercise].

Table 6.0 Biological and Effective Clearance
 | REST |  |  |  |  | STRESS
 | Heart |  | Liver |  |  | Heart |  | Liver
Time | Biological | Effective | Biological | Effective |  | Biological | Effective | Biological | Effective
5 min. | 1.2 | 1.2 | 19.6 | 19.4 |  | 1.5 | 1.5 | 5.9 | 5.8
30 min. | 1.1 | 1.0 | 12.2 | 11.5 |  | 1.4 | 1.3 | 4.5 | 4.2
1 hour | 1.0 | 0.9 | 5.6 | 5.0 |  | 1.4 | 1.2 | 2.4 | 2.1
2 hours | 1.0 | 0.8 | 2.2 | 1.7 |  | 1.2 | 1.0 | 0.9 | 0.7
4 hours | 0.8 | 0.5 | 0.7 | 0.4 |  | 1.0 | 0.6 | 0.3 | 0.2

A study in a dog myocardial ischemia model reported that Technetium Tc99m Sestamibi undergoes myocardial distribution (redistribution), although more slowly and less completely than thallous chloride Tl-201. A study in a dog myocardial infarction model reported that the drug showed no redistribution of any consequence. Definitive human studies to demonstrate possible redistribution have not been reported. In patients with documented myocardial infarction, imaging revealed the infarct up to four hours post dose.

12.3.1 Metabolism

The agent is excreted without any evidence of metabolism.

12.3.2 Elimination

The major pathway for clearance of Tc99m Sestamibi is the hepatobiliary system. Activity from the gall bladder appears in the intestines within one hour of injection. Twenty-seven percent of the injected dose is excreted in the urine, and approximately thirty-three percent of the injected dose is cleared through the feces in 48 hours.

13. NONCLINICAL TOXICOLOGY

13.1 Carcinogenesis, Mutagenesis, Impairment of Fertility

In comparison with most other diagnostic technetium labeled radiopharmaceuticals, the radiation dose to the ovaries (1.5 rads/30 mCi at rest, 1.2 rads/30 mCi at exercise) is high. Minimal exposure (ALARA) is necessary in women of childbearing capability. (See Section 2.)

The active intermediate, Cu(MIBI)4BF4, was evaluated for genotoxic potential in a battery of five tests. No genotoxic activity was observed in the Ames, CHO/HPRT and sister chromatid exchange tests (all in vitro). At cytotoxic concentrations (> 20 µg/mL), an increase in cells with chromosome aberrations was observed in the in vitro human lymphocyte assay. Cu(MIBI)4BF4 did not show genotoxic effects in the in vivo mouse micronucleus test at a dose which caused systemic and bone marrow toxicity (9 mg/kg, > 600 × maximal human dose).

14. CLINICAL STUDIES

CLINICAL TRIALS:

MYOCARDIAL IMAGING: In a trial of rest and stress CARDIOLITE® imaging, the relationship of normal or abnormal perfusion scans and long term cardiac events was evaluated in 521 patients (511 men, 10 women) with stable chest pain. There were 73.9% Caucasians, 25.9% Blacks and 0.2% Asians. The mean age was 59.6 years (range: 29 to 84 years). All patients had a baseline rest and exercise CARDIOLITE® scan and were followed for 13.2 ± 4.9 months (range: 1 to 24 months). Images were correlated with the occurrence of a cardiac event (cardiac death or non-fatal myocardial infarction). In this trial as summarized in Table 7.0, 24/521 (4.6%) had a cardiac event.

Table 7.0 Cardiac Events
Baseline Scan [Note: Similar findings were found in two studies with patients who had pharmacologic stress CARDIOLITE® imaging.] | Proportion of patients with events by scan results | Proportion of scan result in patients with events; N=24 | Proportion of event-free patients by scan result
Normal | 1/206 (0.5%) | 1/24 (4.2%) | 205/206 (99.5%)
Abnormal | 23/315 (7.3%) [p<0.01] | 23/24 (95.8%) | 292/315 (92.7%)

Although patients with normal images had a lower cardiac event rate than those with abnormal images, in all patients with abnormal images it was not possible to predict which patient would be likely to have further cardiac events; i.e., such individuals were not distinguishable from other patients with abnormal images.

The findings were not evaluated for defect location, disease duration, specific vessel involvement or intervening management.

In earlier trials, using a template consisting of the anterior wall, inferior-posterior wall and isolated apex, localization in the anterior or inferior-posterior wall in patients with suspected angina or coronary artery disease was shown. Disease localization isolated to the apex has not been established. In adults, Tc99m Sestamibi has not been studied or evaluated in cardiac disorders other than coronary artery disease.

BREAST IMAGING: MIRALUMA® was evaluated in two multicenter, clinical trials of a total of 673 woman patients. Overall the mean age was 52 (range 23 to 87 years). The racial and ethnic representation was 70% Caucasian, 15% African-American, 14% Hispanic and 1% Asian.

Both clinical studies evaluated women who were referred for further evaluation for either: 1) a mammographically detected (with varying degrees of malignant likelihood) but not palpable breast lesion (study A, n=387, mean age = 54 years), or 2) a palpable breast lesion (study B, n=286, mean age = 50 years). In both studies all patients were scheduled for biopsy.

MIRALUMA® (20 - 30 mCi) was injected intravenously in a vein that was contralateral to the breast lesion in question. Planar imaging was completed with a high resolution collimator with a 10% window centered at 140 KeV, and 128 × 128 matrix. An initial marker image, that was not used in the data analysis, was obtained using a cobalt Co57 point source as a marker of a palpable mass. Images were obtained 5 minutes after injection as follows: lateral image of the affected breast for 10 minutes, lateral image of the contralateral breast for 10 minutes, and an anterior image of both breasts for 10 minutes. For the lateral image the patients were positioned in a prone position. For the anterior image, the patients were supine. The MIRALUMA® scintigraphic images were read in a randomized method by two groups of three blinded readers. MIRALUMA® uptake was scored as: normal (no uptake), equivocal, low, moderate, or high uptake. The results of MIRALUMA® images and mammography were analyzed in comparison to histopathologic findings of malignant or non-malignant disease.

As shown in Table 8.0 for the 483 evaluable patients, the sensitivity and specificity of any degree of MIRALUMA® uptake appear to vary with the presence or absence of palpable mass.

TABLE 8.0 Overall MIRALUMA® Blinded Results of Target Lesions [Excludes all discordant lesions not identified at entry and excludes 25 equivocal interpretations from Study A and 32 equivocal interpretations from Study B (see Tables 9.0 and 10.0)] Identified at Study Entry [Some patients had more than one target lesion]
STATISTIC | Study A Non-Palpable Mass and an Abnormal Mammogram | Study B Palpable Mass
Number of Patients and Lesions | N=277 Patients with 300 Lesions | N=206 Patients with 240 Lesions
Sensitivity | 52(42,62) [Median and approximated 95% Confidence Interval] | 76(67,83)
Specificity | 94(89,96) | 85(77,91)
PPV [PPV= Positive Predict Value; NPV= Negative Predict Value] | 79(67,88) | 83(74,89)
NPV | 80(74,85) | 78(69,84)
Agreement | 80(75,85) | 80(75,85)
Prevalence | 32(27,37) | 49(43,56)

In a separate retrospective subset analyses of 259 patients with dense (heterogeneously/extremely dense) and 275 patients with fatty (almost entirely fat/numerous vague densities) breast tissue, the MIRALUMA® results were similar. Overall, the studies were not designed to compare the performance of MIRALUMA® with the performance of mammography in patients with breast densities or other coexistent breast tissue disorders.

In general the histology seems to correlate with the degree of MIRALUMA® uptake. As shown in Tables 9.0 and 10.0, the majority of the normal MIRALUMA® images are associated with non-malignant tissue (78-81%) and the majority of low, moderate or high uptake MIRALUMA® images are associated with malignant disease (79-83%). In an individual patient, however, the intensity of MIRALUMA® uptake can not be used to confirm the presence or absence of malignancy. Equivocal results do not have a correlation with histology.

TABLE 9.0 Degree of MIRALUMA® Breast Imaging Uptake in Comparison to Histopathology Results in Patients with Mammographically Detected Non-Palpable Lesions [Median finding for 3 blinded readers] (Study A)
 | Normal Uptake N = 249 lesions | Equivocal Uptake N = 25 lesions | Low, Moderate or High Uptake N = 66 lesions
Non-malignant [Includes benign tissue, fibroadenoma, benign intramammary nodes, radial scar.] | 201 (81%) | 14 (56%) | 14 (21%)
Malignant | 48 (19%) | 11 (44%) | 52 (79%)

TABLE 10.0 Degree of MIRALUMA® Breast Imaging Uptake in Comparison to Histopathology Results in Patients with Palpable Lesions [Median finding for 3 blinded readers] (Study B)
 | Normal Uptake N = 129 lesions | Equivocal Uptake N = 32 lesions | Low, Moderate or High Uptake N = 115 lesions
Non-malignant [Includes benign tissue, fibroadenoma, benign intramammary nodes, radial scar.] | 100 (78%) | 19 (59%) | 20 (17%)
Malignant | 29 (22%) | 13 (41%) | 95 (83%)

An estimate of the likelihood of malignancy based on the MIRALUMA® uptake score in combination with the mammographic score has not been studied.

In these two studies approximately 150 additional, non-biopsied lesions were found to be positive after MIRALUMA® imaging. These lesions were identified in sites that did not physically correlate with identified entry criteria mammographic lesions and these lesions were not palpable. These lesions were not biopsied. Whether these lesions were benign or malignant is not known. MIRALUMA® uptake can occur in both benign and malignant disease. THE CLINICAL USEFULNESS OF A POSITIVE MIRALUMA® IMAGE IN THE ABSENCE OF AN ABNORMAL MAMMOGRAM OR A PALPABLE LESION IS NOT KNOWN.

16. HOW SUPPLIED/STORAGE AND HANDLING

CARDIOLITE®, Kit for the Preparation of Technetium Tc99m Sestamibi for Injection is supplied as a 5 mL vial in kits of five (5) vials (NDC # 11994-001-55) and twenty (20) vials (NDC # 11994-001-20), sterile and non-pyrogenic.

The patient dose should be measured by a suitable radioactivity calibration system immediately prior to patient administration. Radiochemical purity should be checked prior to patient administration.

Parenteral drug products should be inspected visually for particulate matter and discoloration prior to administration whenever solution and container permit.

Prior to lyophilization the pH is between 5.3-5.9. The contents of the vial are lyophilized and stored under nitrogen. Store at 15-25°C (59-77° F) before and after reconstitution.

Technetium Tc99m Sestamibi contains no preservatives. Included in each five (5) vial kit is one (1) package insert, six (6) vial shield labels and six (6) radiation warning labels. Included in each twenty (20) vial kit is one (1) package insert, twenty four (24) vial shield labels and twenty four (24) radiation warning labels.

This reagent kit is approved for distribution to persons licensed pursuant to the Code of Massachusetts Regulations 105 CMR 120.500 for the uses listed in 105 CMR 120.547 or 120.552, or under equivalent regulations of the U.S. Nuclear Regulatory Commission, Agreement States or Licensing States.

17. PATIENT COUNSELING INFORMATION

CARDIOLITE® and MIRALUMA® are different names for the same drug. Patients should be advised to inform their health care provider if they had an allergic reaction to either drug or if they had an imaging study with either drug.

Lactation: Interruption of breastfeeding after exposure to Technetium Tc99m Sestamibi is not necessary, however, a lactating woman should be advised to consider restricting close contact with her breast fed infant to a maximum of 5 hours in the 24 hour period after Technetium Tc99m Sestamibi administration in order to minimize radiation exposure [see Use in Specific Populations (8.2)].

Distributed by:
Lantheus Medical Imaging®
331 Treble Cove Road
N. Billerica, Massachusetts 01862 USA
For Ordering Tel: Toll Free: 800-299-3431
All Other Business: 800-362-2668
(For Massachusetts and International call 978-667-9531)

513121-0619

PRINCIPAL DISPLAY PANEL - 5 Vial Box

Lantheus
Medical Imaging®

Cardiolite®

Kit for the Preparation of Technetium Tc99m Sestamibi for Injection

CONTENTS AND STORAGE CONDITIONS:
1 Package Insert, 12 Radiation Labels and 5 Vials, each containing:
Tetrakis (2-methoxy isobutyl isonitrile) Copper (I) tetrafluoroborate - 1.0 mg
Stannous Chloride Dihydrate - 0.075 mg; L-Cysteine Hydrochloride
Monohydrate - 1.0 mg; Sodium Citrate Dihydrate - 2.6 mg; Mannitol - 20 mg
Store at 15-25°C (59-77°F).

CONTAINS NO PRESERVATIVE. See Package Insert for dosage information.
Reconstitute with additive-free Tc99m and store at 15-25°C (59-77°F).
Use within 6 hours of reconstitution.